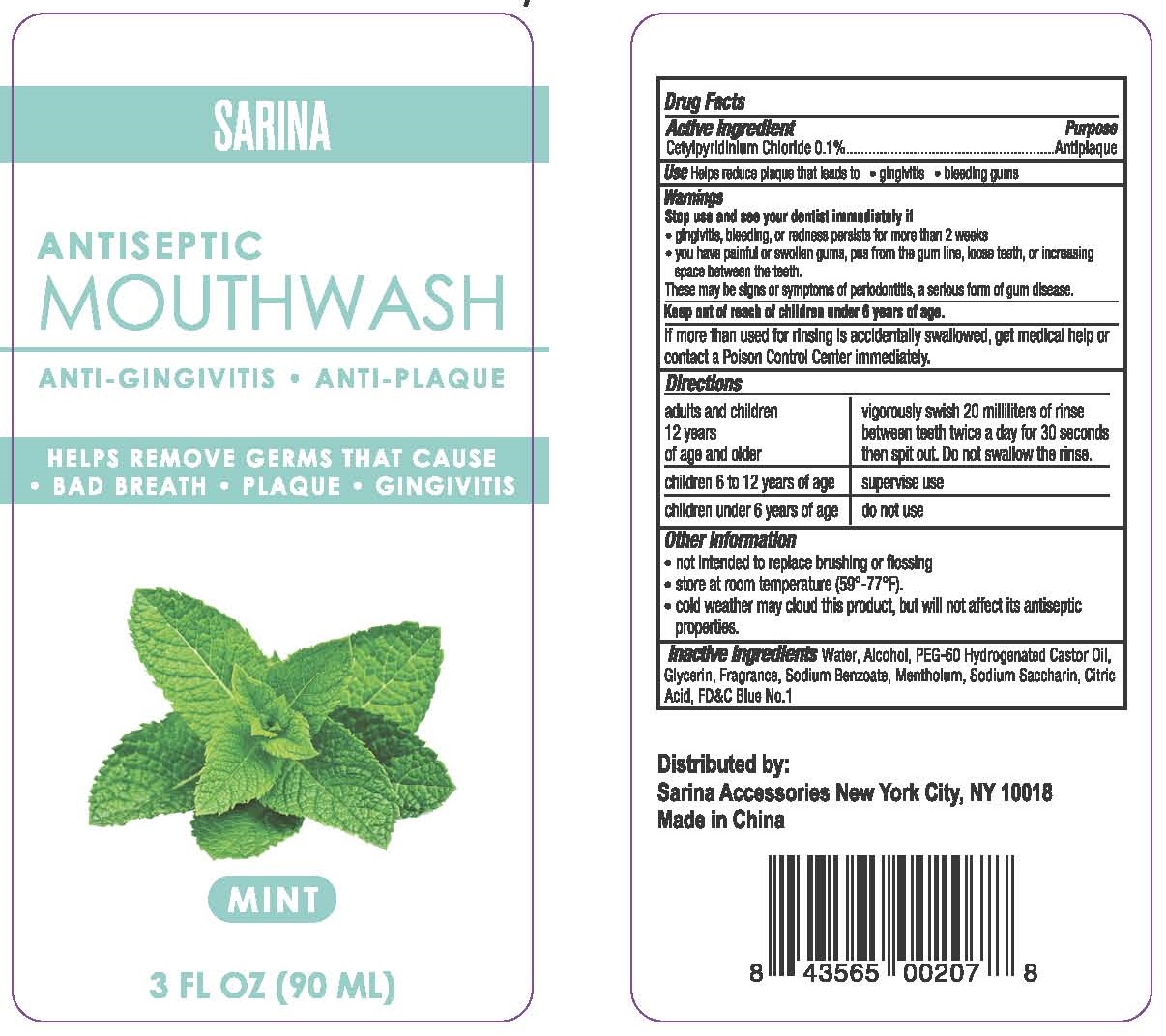 DRUG LABEL: SARINA
NDC: 90106-003 | Form: LIQUID
Manufacturer: Sarina Accessories, LLC
Category: otc | Type: HUMAN OTC DRUG LABEL
Date: 20200825

ACTIVE INGREDIENTS: CETYLPYRIDINIUM CHLORIDE 1 mg/100 mL
INACTIVE INGREDIENTS: WATER; GLYCERIN; SODIUM BENZOATE; ALCOHOL; SACCHARIN SODIUM; CITRIC ACID MONOHYDRATE; FD&C BLUE NO. 1; PEG-60 HYDROGENATED CASTOR OIL; MENTHOL

SARINA ANTISEPTIC MOUTHWASH

Active ingredients

Cetylpyridinium Chloride 0.1%.

Purpose

Antiplaque

Use

Helps reduce plaque that leads to

- ginivitis
- bleeding gums

Warnings

Stop use and see your dentist immediately if

- gingivitis, bleeding, or redness persists for more than 2 weeks
- you have painful or swollen gums, pus from the gum line, loose teeth, or increasing space between the teeth.

These may be signs or symptoms of periodontitis, a serious form of gum disease.

Keep out of reach of children under 6 years of age.

If more than used for rinsing is accidentally swallowed, get medical help or contact a Poison Control Center immediately.

Directions

adults and children 12 years of age and older | vigorously swish 20 milliliters of rinse between teeth twice a day for 30 seconds then spit out. Do not swallow the rinse
children 6 to 12 years of age | supervise use
children under 6 years of age | do not use

Other information

- not intended to replace brushing or flossing
- store at room temperature (59°-77°F).
- cold weather may cloud this product, but will not affect its antiseptic properties.

Inactive ingredients

Water, Alcohol, PEG-60 Hydrogenated Castor Oil，Glycerin，Fragrance，Sodium Benzoate，Mentholum，Sodium Saccharin，Citric Acid，FD&C Blue No.1